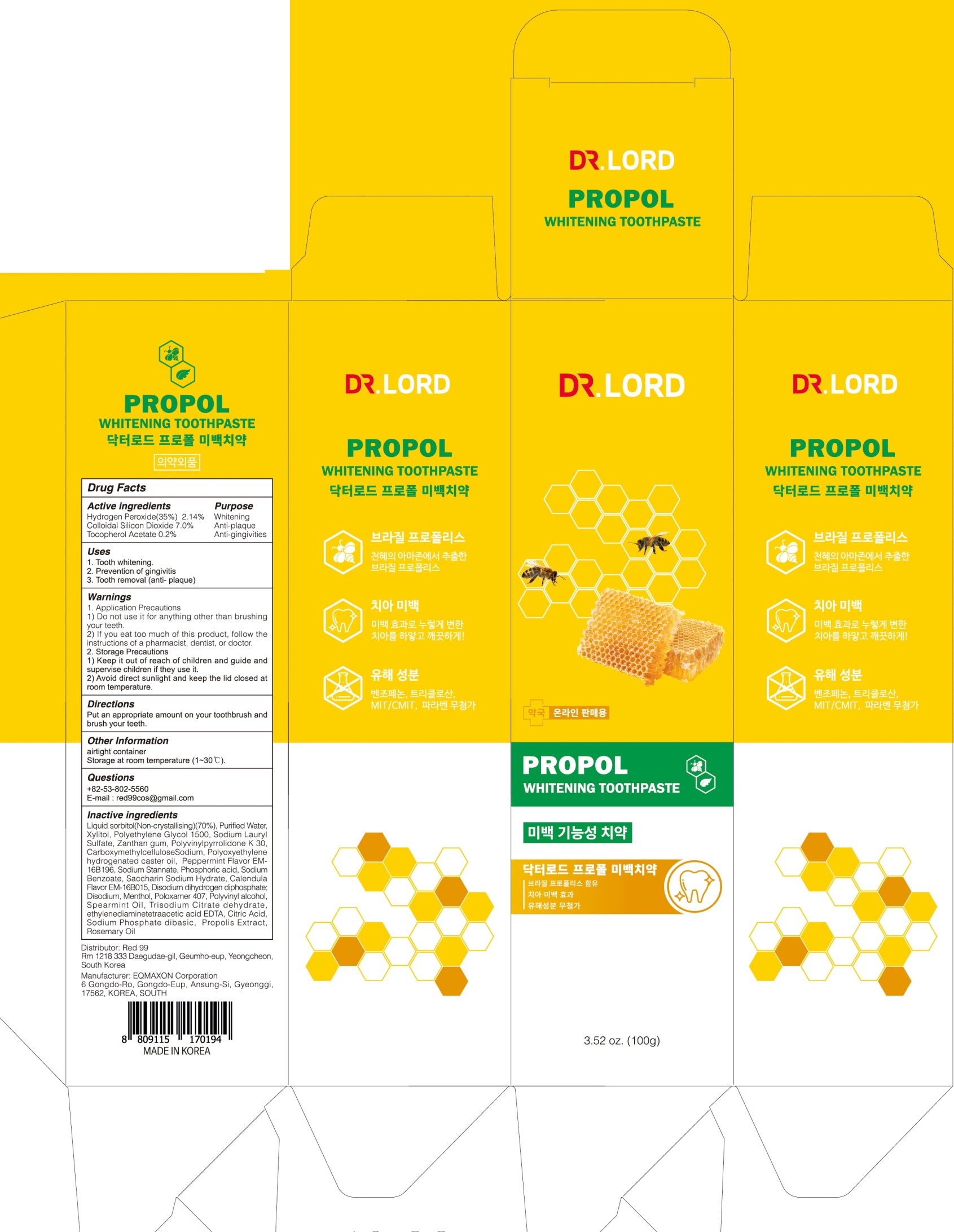 DRUG LABEL: Dr.LORD Propol Whitening Tooth
NDC: 82656-020 | Form: PASTE, DENTIFRICE
Manufacturer: Red 99
Category: otc | Type: HUMAN OTC DRUG LABEL
Date: 20220406

ACTIVE INGREDIENTS: Silicon Dioxide 7.0 g/100 g; Hydrogen Peroxide 2.14 g/100 g; .ALPHA.-TOCOPHEROL ACETATE 0.2 g/100 g
INACTIVE INGREDIENTS: Sorbitol; Water; Xylitol

ACTIVE INGREDIENTS

Hydrogen Peroxide(35%) 2.14%
Colloidal Silicon Dioxide 7.0%
Tocopherol Acetate 0.2%

INACTIVE INGREDIENTS

Liquid sorbitol(Non-crystallising)(70%), Purified Water, Xylitol, Polyethylene Glycol 1500, Sodium Lauryl Sulfate, Zanthan gum, Polyvinylpyrrolidone K 30, CarboxymethylcelluloseSodium, Polyoxyethylene hydrogenated caster oil, Peppermint Flavor EM-16B196, Sodium Stannate, Phosphoric acid, Sodium Benzoate, Saccharin Sodium Hydrate, Calendula Flavor EM-16B015, Disodium dihydrogen diphosphate; Disodium, Menthol, Poloxamer 407, Polyvinyl alcohol, Spearmint Oil, Trisodium Citrate dehydrate, ethylenediaminetetraacetic acid EDTA, Citric Acid, Sodium Phosphate dibasic, Propolis Extract, Rosemary Oil

PURPOSE

Whitening
Anti-plaque
Anti-gingivities

WARNINGS

1. Application Precautions
1) Do not use it for anything other than brushing your teeth.
2) If you eat too much of this product, follow the instructions of a pharmacist, dentist, or doctor.
2. Storage Precautions
1) Keep it out of reach of children and guide and supervise children if they use it.
2) Avoid direct sunlight and keep the lid closed at room temperature.

KEEP OUT OF REACH OF CHILDREN

Keep it out of reach of children and guide and supervise children if they use it.

Uses

1. Tooth whitening.
2. Prevention of gingivitis
3. Tooth removal (anti- plaque)

Directions

Put an appropriate amount on your toothbrush and brush your teeth.

Other Information

airtight container
Storage at room temperature (1~30℃)

Questions

Telephone Number : +82-53-802-5560
E-mail : red99cos@gmail.com